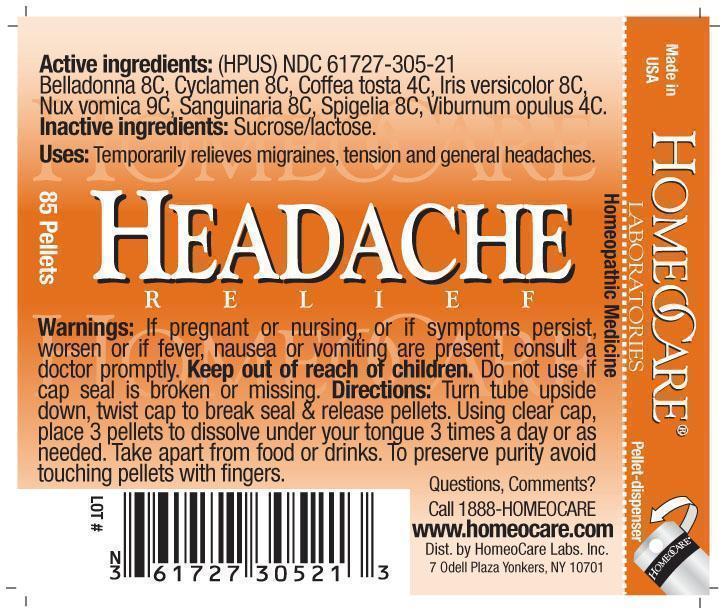 DRUG LABEL: Headache Relief
NDC: 61727-305 | Form: PELLET
Manufacturer: Homeocare Laboratories
Category: homeopathic | Type: HUMAN OTC DRUG LABEL
Date: 20260112

ACTIVE INGREDIENTS: ATROPA BELLADONNA 8 [hp_C]/4 g; CYCLAMEN PURPURASCENS TUBER 8 [hp_C]/4 g; COFFEA ARABICA SEED, ROASTED 4 [hp_C]/4 g; IRIS VERSICOLOR ROOT 8 [hp_C]/4 g; STRYCHNOS NUX-VOMICA SEED 9 [hp_C]/4 g; SANGUINARIA CANADENSIS ROOT 8 [hp_C]/4 g; SPIGELIA MARILANDICA ROOT 8 [hp_C]/4 g; VIBURNUM OPULUS BARK 4 [hp_C]/4 g
INACTIVE INGREDIENTS: SUCROSE; LACTOSE

Headache Relief

Active Ingredients:

Belladonna 8C, Cyclamen 8C, Coffea tosta 4C, Iris versicolor 8C, Nux vomica 9C, Sanguinaria 8C, Spigelia 8C, Viburnum opulus 4C.

Inactive Ingredients:

Sucrose/lactose.

Keep out of reach of children.

Purpose:

Temporarily relieves migraines, tension and general headaches.

Warnings:

If pregnant or nursing, or if symptoms persist, worsen or if fever, nausea or vomiting are present, consult a doctor promptly. Keep out of reach of children. Do not use if cap seal is broken or missing.

Indications & Usage:

Turn turn upside down, twist cap to break seal & release pellets. Using clear cap, place 3 pellets to dissolve under your tongue 3 times a day or as needed. Take apart from food or drinks. To preserve purity avoid touching pellets with fingers.

Dosage & Administration:

Turn turn upside down, twist cap to break seal & release pellets. Using clear cap, place 3 pellets to dissolve under your tongue 3 times a day or as needed. Take apart from food or drinks. To preserve purity avoid touching pellets with fingers.